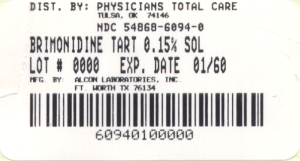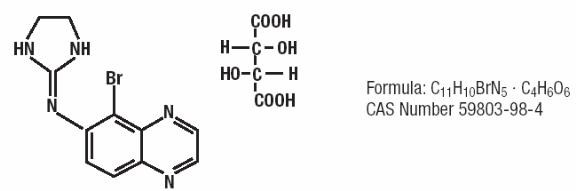 DRUG LABEL: Brimonidine Tartrate
NDC: 54868-6094 | Form: SOLUTION
Manufacturer: Physicians Total Care, Inc.
Category: prescription | Type: HUMAN PRESCRIPTION DRUG LABEL
Date: 20100112

ACTIVE INGREDIENTS: BRIMONIDINE TARTRATE 1.5 mg/1 mL
INACTIVE INGREDIENTS: POVIDONE; BORIC ACID; SODIUM BORATE; CALCIUM CHLORIDE; MAGNESIUM CHLORIDE; POTASSIUM CHLORIDE; MANNITOL; SODIUM CHLORIDE; WATER; HYDROCHLORIC ACID; SODIUM HYDROXIDE

DESCRIPTION

Brimonidine Tartrate Ophthalmic Solution, 0.15% (1.5 mg brimonidine tartrate per mL equivalent to 1.0 mg brimonidine free base per mL) is a relatively selective alpha-2-adrenergic agonist for ophthalmic use. The chemical name of brimonidine tartrate is 5-bromo-6-(2-imidazolidinylideneamino) quinoxaline L-tartrate. It is an off-white to pale yellow powder. It has a molecular weight of 442.24 as the tartrate salt, and is both soluble in water (1.5 mg/mL) and in the product vehicle (3.0 mg/mL) at pH 7.2. The structural formula is:

In solution, Brimonidine Tartrate Ophthalmic Solution, 0.15% has a clear, greenish-yellow color. It has an osmolality of 250 - 350 mOsmol/kg and a pH of 6.6-7.4.

Each mL of Brimonidine Tartrate Ophthalmic Solution, 0.15% contains: Active ingredient: brimonidine tartrate 0.15% (1.5 mg/mL) Inactives: povidone; boric acid; sodium borate; calcium chloride; magnesium chloride; potassium chloride; mannitol; sodium chloride; POLYQUAD* 0.001% (0.01 mg/mL); purified water; with hydrochloric acid and/or sodium hydroxide to adjust pH.

CLINICAL PHARMACOLOGY

Mechanism of Action:

Brimonidine Tartrate Ophthalmic Solution, 0.15% is an alpha-2 adrenergic receptor agonist. It has a peak ocular hypotensive effect occurring at two hours post-dosing. Fluorophotometric studies in animals and humans suggest that brimonidine tartrate has a dual mechanism of action by reducing aqueous humor production and increasing uveoscleral outflow.

Pharmacokinetics:

In a pharmacokinetic study, 14 healthy subjects (4 males and 10 females) received a single topical ocular administration of Brimonidine Tartrate Ophthalmic Solution, 0.15%, one drop per eye. The peak plasma concentrations (Cmax) and AUC 0-inf were 73 ± 19 pg/mL and 375 ± 89 pg•hr/mL, respectively. Tmax was 1.7 ± 0.7 hours after dosing. The systemic half-life was approximately 2.1 hours.

Brimonidine is metabolized primarily by the liver. In vitro metabolism data from human microsomal fractions and liver slices indicate that brimonidine undergoes extensive hepatic metabolism.

Urinary excretion is the major route of elimination of brimonidine and its metabolites. Approximately 87% of an orally administered radioactive dose of brimonidine was eliminated within 120 hours, with 74% of the radioactivity recovered in the urine.

Special Populations

Brimonidine Tartrate Ophthalmic Solution, 0.15% has not been studied in patients with hepatic or renal impairment. Because of the low systemic drug exposure following topical ocular administration of Brimonidine Tartrate Ophthalmic Solution, 0.15%, no dose adjustment is necessary when treating patients with hepatic or renal impairment.

Clinical Evaluations:

Elevated IOP presents a major risk factor in glaucomatous field loss. The higher the level of IOP, the greater the likelihood of optic nerve damage and visual field loss. Brimonidine tartrate has the action of lowering intraocular pressure with minimal effect on cardiovascular and pulmonary parameters.

A clinical study was conducted to evaluate the safety and efficacy of Brimonidine Tartrate Ophthalmic Solution, 0.15% compared to Alphagan® P** administered three-times-daily in patients with open-angle glaucoma or ocular hypertension. The results indicated that Brimonidine Tartrate Ophthalmic Solution, 0.15% is equivalent in IOP-lowering effect to Alphagan® P (brimonidine tartrate ophthalmic solution), 0.15%, and effectively lowers IOP in patients with open-angle glaucoma or ocular hypertension by 2 - 6 mm Hg.

INDICATIONS AND USAGE

Brimonidine Tartrate Ophthalmic Solution, 0.15% is indicated for the lowering of intraocular pressure in patients with open-angle glaucoma or ocular hypertension.

CONTRAINDICATIONS

Brimonidine Tartrate Ophthalmic Solution, 0.15% is contraindicated in patients with hypersensitivity to brimonidine tartrate or any component of this medication. It is also contraindicated in patients receiving monoamine oxidase (MAO) inhibitor therapy.

PRECAUTIONS

General:

Although Brimonidine Tartrate Ophthalmic Solution, 0.15% had minimal effect on the blood pressure of patients in clinical studies, caution should be exercised in treating patients with severe cardiovascular disease.

Brimonidine Tartrate Ophthalmic Solution, 0.15% has not been studied in patients with hepatic or renal impairment; caution should be used in treating such patients.

Brimonidine Tartrate Ophthalmic Solution, 0.15% should be used with caution in patients with depression, cerebral or coronary insufficiency, Raynaud's phenomenon, orthostatic hypotension, or thromboangiitis obliterans. Patients prescribed IOP-lowering medication should be routinely monitored for IOP.

Information for Patients:

As with other drugs in this class, Brimonidine Tartrate Ophthalmic Solution, 0.15% may cause fatigue and/or drowsiness in some patients. Patients who engage in hazardous activities should be cautioned of the potential for a decrease in mental alertness.

Drug Interactions:

Although specific drug interaction studies have not been conducted with Brimonidine Tartrate Ophthalmic Solution, 0.15%, the possibility of an additive or potentiating effect with CNS depressants (alcohol, barbiturates, opiates, sedatives, or anesthetics) should be considered. Alpha-2 agonists, as a class, may reduce pulse and blood pressure. Caution in using concomitant drugs such as beta-blockers (ophthalmic and systemic), anti-hypertensives and/or cardiac glycosides is advised.

Tricyclic antidepressants have been reported to blunt the hypotensive effect of systemic clonidine. It is not known whether the concurrent use of these agents with Brimonidine Tartrate Ophthalmic Solution, 0.15% in humans can interfere with its IOP-lowering effect. No data on the level of circulating catecholamines after Brimonidine Tartrate Ophthalmic Solution, 0.15% administration are available. Caution, however, is advised in patients taking tricyclic antidepressants, which can affect the metabolism and uptake of circulating amines.

Carcinogenesis, Mutagenesis, and Impairment of Fertility:

No compound-related carcinogenic effects were observed in either mice or rats following a 21-month and a 24-month study, respectively. In these studies, dietary administration of brimonidine tartrate at doses up to 2.5 mg/kg/day in mice and 1.0 mg/kg/day in rats achieved 60 and 50 times, respectively, the plasma drug concentration estimated in humans treated with one drop of Brimonidine Tartrate Ophthalmic Solution, 0.15% into both eyes.

Brimonidine tartrate was not mutagenic or cytogenic in a series of in vitro and in vivo studies including the Ames test, chromosomal aberration assay in Chinese hamster ovary (CHO) cells, a host-mediated assay and cytogenic studies in mice, and dominant lethal assay.

Pregnancy: Teratogenic Effects: Pregnancy Category: B

Reproductive studies performed in rats and rabbits with oral doses of 0.66 mg base/kg revealed no evidence of harm to the fetus due to Brimonidine Tartrate Ophthalmic Solution, 0.15%. Dosing at this level produced an exposure in rats and rabbits that is 80 and 40 times higher than the exposure seen in humans, respectively.

There are no adequate and well-controlled studies in pregnant women. In animal studies, brimonidine crossed the placenta and entered into the fetal circulation to a limited extent. Brimonidine Tartrate Ophthalmic Solution, 0.15% should be used during pregnancy only if the potential benefit to the mother justifies the potential risk to the fetus.

Nursing Mothers:

It is not known whether this drug is excreted in human milk. In animal studies, brimonidine tartrate was excreted in breast milk. A decision should be made whether to discontinue nursing or to discontinue the drug, taking into account the importance of the drug to the mother.

Pediatric Use:

In a well-controlled clinical study conducted in pediatric glaucoma patients (ages 2 to 7 years) the most commonly observed adverse events with brimonidine tartrate ophthalmic solution 0.2% dosed three-times-daily were somnolence (50%-83% in patients ages 2 to 6 years) and decreased alertness. In pediatric patients 7 years of age or older (>20 kg), somnolence appears to occur less frequently (25%). Approximately 16% of patients on brimonidine tartrate ophthalmic solution discontinued from the study due to somnolence.

The safety and effectiveness of brimonidine tartrate ophthalmic solution have not been studied in pediatric patients below the age of 2 years. Brimonidine tartrate ophthalmic solution is not recommended for use in pediatric patients under the age of 2 years. (Also refer to ADVERSE REACTIONS section.)

Geriatric Use:

No overall differences in safety or effectiveness have been observed between elderly and other adult patients.

ADVERSE REACTIONS

Adverse events occurring in approximately 10-20% of the subjects included: allergic conjunctivitis, conjunctival hyperemia, and eye pruritis.

Adverse events occurring in approximately 5-9% of the subjects included: burning sensation, conjunctival folliculosis, hypertension, ocular allergic reaction, oral dryness, and visual disturbance.

Events occurring in approximately 1-4% of subjects included: allergic reaction, arthralgia, arthritis, asthenia, blepharitis, blepharoconjunctivitis, blurred vision, bronchitis, cataract, chest pain, conjunctival edema, conjunctival hemorrhage, conjunctivitis, cough, dizziness, diabetes mellitus, dyspepsia, dyspnea, epiphora, eye discharge, eye dryness, eye irritation, eye pain, eyelid edema, eyelid erythema, fatigue, flu syndrome, follicular conjunctivitis, foreign body sensation, gastrointestinal disorder, headache, hypercholesterolemia, hypotension, infection, insomnia, joint disorder, keratitis, lid disorder, osteoporosis, pharyngitis, photophobia, rash, rhinitis, sinus infection, sinusitis, somnolence, stinging, superficial punctate keratopathy, tearing, visual field defect, vitreous detachment, vitreous disorder, vitreous floaters, and worsened visual acuity.

The following events were reported in less than 1% of subjects: corneal erosion, nasal dryness, and taste perversion.

The following events have been identified during post-marketing use of brimonidine tartrate ophthalmic solutions in clinical practice. Because they are reported voluntarily from a population of unknown size, estimates of frequency cannot be made. The events, which have been chosen for inclusion due to either their seriousness, frequency of reporting, possible causal connection to brimonidine tartrate ophthalmic solutions, or a combination of these factors, include: bradycardia; iritis; miosis; skin reactions (including erythema, eyelid pruritis, rash, and vasodilation); and tachycardia. Apnea, bradycardia, hypotension, hypothermia, hypotonia, and somnolence have been reported in infants receiving brimonidine tartrate ophthalmic solutions.

OVERDOSAGE

No information is available on overdosage in humans. Treatment of an oral overdose includes supportive and symptomatic therapy; a patent airway should be maintained.

DOSAGE AND ADMINISTRATION

The recommended dose is one drop of Brimonidine Tartrate Ophthalmic Solution, 0.15% in the affected eye(s) three-times-daily, approximately 8 hours apart.

Brimonidine Tartrate Ophthalmic Solution, 0.15% may be used concomitantly with other topical ophthalmic drug products to lower intraocular pressure. If more than one topical ophthalmic product is being used, the products should be administered at least 5 minutes apart.

HOW SUPPLIED

Brimonidine Tartrate Ophthalmic Solution, 0.15% is supplied sterile in opaque white LDPE plastic bottles and natural tips with purple polypropylene caps as follows:

10 mL in 10 mL bottle NDC 54868-6094-0

Storage: Store at 15°-25° C (59° - 77°F).

Rx Only

Distributed by:

Falcon Pharmaceuticals, Ltd.

Fort Worth, Texas 76134

Manufactured by:

Alcon Laboratories, Inc.

Fort Worth, Texas 76134

Printed in USA

*POLYQUAD is a registered trademark of Alcon Research, Ltd.

**ALPHAGAN P is a registered trademark of Allergan, Inc.

349040-1008

PRINCIPAL DISPLAY PANEL

Brimonidine Tartrate Opthalmic Solution